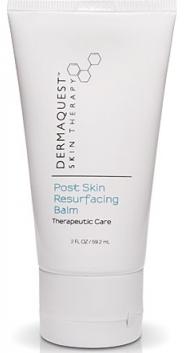 DRUG LABEL: Dermaquest Skin Therapy Post-Skin Resurfacing Balm
NDC: 62742-4051 | Form: CREAM
Manufacturer: Allure Labs, Inc.
Category: otc | Type: HUMAN OTC DRUG LABEL
Date: 20100819

ACTIVE INGREDIENTS: HYDROCORTISONE 10 mg/1 mL

Drug Facts

ACTIVE INGREDIENT:

Hydrocortisone 1%

PURPOSE:

Anti-itch

USES:

- promotes healing of itchy skin
- keeps skin hydrated

WARNINGS:

For external use only.

Ask a doctor if bleeding occurs or conditions worsens

Keep out of reach of chilren.

If swallowed get medical help or contact a Poison Control Center right away.

DIRECTIONS:

Apply to the skin as instructed by your skincare professional to keep the skin hydrated and to promote healing.

INACTIVE INGREDIENTS:

Petrolatum, Tocopheryl Acetate (Vitamin E), Carthamus Tinctorius (Safflower) Seed Oil, Ubiquinone (Co-Enzyme Q10), Zinc Oxide (Cl 77947), Titanium Dioxide (Cl 77891), Ascorbyl Palmiate (Vitamin C), Glycosaminoglycans.

PACKAGE LABEL

DISTRIBUTOR:

DermaQuest, Inc.

Hayward, CA

dermaquestinc.com

IMAGE OF PRINCIPAL DISPLAY PANEL: